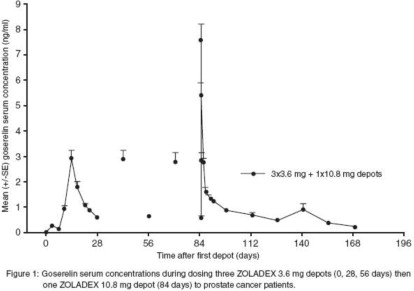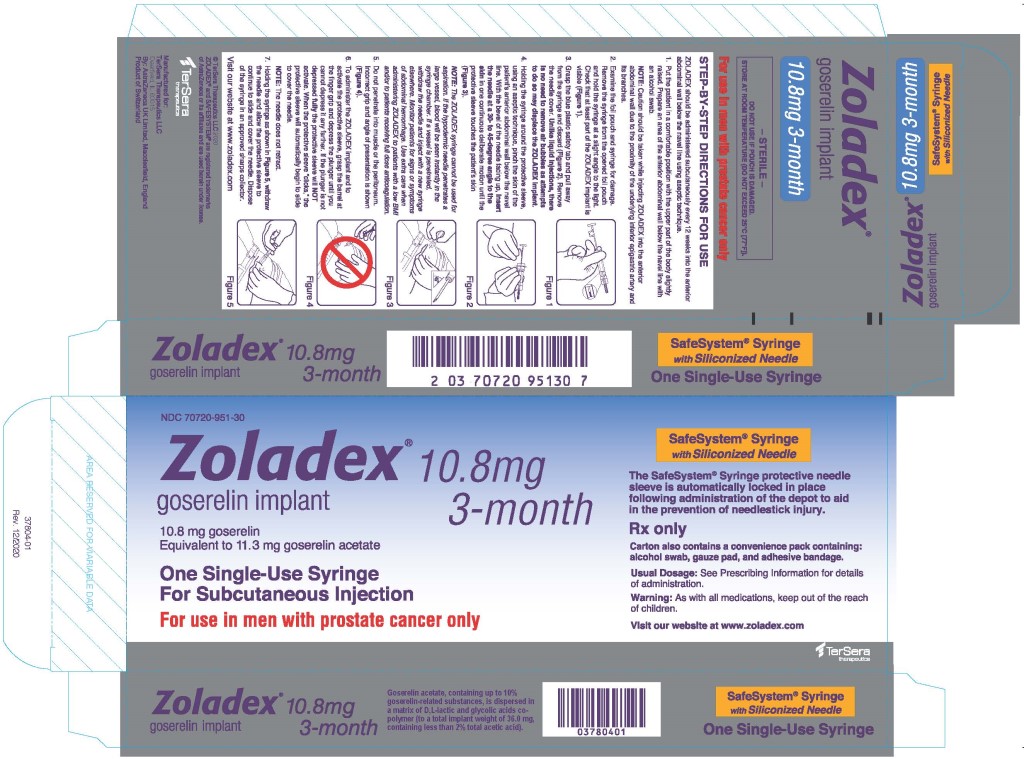 DRUG LABEL: ZOLADEX
NDC: 70720-951 | Form: IMPLANT
Manufacturer: TerSera Therapeutics LLC
Category: prescription | Type: HUMAN PRESCRIPTION DRUG LABEL
Date: 20250924

ACTIVE INGREDIENTS: goserelin acetate 10.8 mg/1 1
INACTIVE INGREDIENTS: Glycolic Acid; Lactic Acid, DL-

HIGHLIGHTS OF PRESCRIBING INFORMATION

These highlights do not include all the information needed to use ZOLADEX safely and effectively.
See full prescribing information for ZOLADEX.
ZOLADEX® (goserelin implant) 10.8 mg
Initial U.S. Approval: 1996

RECENT MAJOR CHANGES

Warnings and Precautions (5.5) | 9/2025

1 INDICATIONS AND USAGE

ZOLADEX is a Gonadotropin Releasing Hormone (GnRH) agonist indicated for:

- Use in combination with flutamide for the management of locally confined carcinoma of the prostate (1.1)
- Use as palliative treatment of advanced carcinoma of the prostate (1.2)

2 DOSAGE AND ADMINISTRATION

ZOLADEX, at a dose of 10.8 mg, should be administered subcutaneously every 12 weeks into the anterior abdominal wall below the navel line (2.1, 2.5)

3 DOSAGE FORMS AND STRENGTHS

Implant 10.8 mg (3)

4 CONTRAINDICATIONS

- Hypersensitivity (4.1)
- Pregnancy (4.2, 8.1)

5 WARNINGS AND PRECAUTIONS

- Tumor Flare Phenomenon: Transient worsening of tumor symptoms may occur during the first few weeks of treatment with ZOLADEX, which may include ureteral obstruction and spinal cord compression. Monitor patients at risk for complications of tumor flare (5.1, 6.1)
- Hypersensitivity: Systemic hypersensitivity has been reported in patients receiving goserelin implants (4.1, 5.2)
- Hyperglycemia and Diabetes: Hyperglycemia and an increased risk of developing diabetes have been reported in men receiving GnRH analogs. Monitor blood glucose level and manage according to current clinical practice (5.3)
- Cardiovascular Diseases: Increased risk of myocardial infarction, sudden cardiac death and stroke has been reported in association with use of GnRH analogs in men. Monitor for cardiovascular disease and manage according to current clinical practice (5.4)
- Severe Cutaneous Adverse Reactions: ZOLADEX can cause severe cutaneous adverse reactions (SCARs), including Stevens-Johnson syndrome/toxic epidermal necrolysis. Interrupt ZOLADEX if signs or symptoms of SCARs develop. Permanently discontinue ZOLADEX if SCARs are confirmed. (5.5)
- Effect on QT/QTc Interval: Androgen deprivation therapy may prolong the QT interval. Consider risks and benefits (5.6)
- Injection Site Injury: Injection site injury and vascular injury have been reported during administration (5.7)

6 ADVERSE REACTIONS

The most common, clinically significant adverse reactions occurring in >10% of men: hot flashes, sexual dysfunction, decreased erections and lower urinary tract symptoms (6)

Tumor flare can occur on the initiation of ZOLADEX therapy (5.1, 6.1)

To report SUSPECTED ADVERSE REACTIONS, contact TerSera Therapeutics at 1-844-334-4035 or FDA at 1-800-FDA-1088 or www.fda.gov/medwatch.

7 DRUG INTERACTIONS

- None

8 USE IN SPECIFIC POPULATIONS

- Nursing mothers: Discontinue drug or nursing taking into account the importance of drug to the mother (8.3)
- No information available for use in Pediatric patients (8.4)
- Geriatric (8.5)
- Renal and Hepatic Impairment: No dose adjustment is necessary (2.3, 8.6, 8.7)

FULL PRESCRIBING INFORMATION

1 INDICATIONS AND USAGE

1.1 Stage B2-C Prostatic Carcinoma

ZOLADEX is indicated for use in combination with flutamide for the management of locally confined Stage T2b-T4 (Stage B2-C) carcinoma of the prostate. Treatment with ZOLADEX and flutamide should start 8 weeks prior to initiating radiation therapy and continue during radiation therapy [see Dosage and Administration (2.1) and Clinical Studies (14.1)].

1.2 Prostatic Carcinoma

ZOLADEX is indicated in the palliative treatment of advanced carcinoma of the prostate [see Dosage and Administration (2.2) and Clinical Studies (14.2)].

In controlled studies of patients with advanced prostatic cancer comparing ZOLADEX 3.6 mg to orchiectomy, the long-term endocrine responses and objective responses were similar between the two treatment arms. Additionally, duration of survival was similar between the two treatment arms in a major comparative trial.

In controlled studies of patients with advanced prostatic cancer, ZOLADEX 10.8 mg implant produced pharmacodynamically similar effect in terms of suppression of serum testosterone to that achieved with ZOLADEX 3.6 mg implant. Clinical outcome similar to that produced with the use of the ZOLADEX 3.6 mg implant administered every 28 days is predicted with the ZOLADEX 10.8 mg implant administered every 12 weeks.

The automatic safety feature of the syringe aids in the prevention of needlestick injury.

2 DOSAGE AND ADMINISTRATION

ZOLADEX, at a dose of 10.8 mg, should be administered subcutaneously every 12 weeks into the anterior abdominal wall below the navel line using an aseptic technique under the supervision of a physician [see Dosage and Administration (2.5)].

While a delay of a few days is permissible, every effort should be made to adhere to the 12-week schedule.

2.1 Stage B2-C Prostatic Carcinoma

When ZOLADEX is given in combination with radiotherapy and flutamide for patients with Stage T2b-T4 (Stage B2-C) prostatic carcinoma, treatment should be started 8 weeks prior to initiating radiotherapy and should continue during radiation therapy. A treatment regimen using one ZOLADEX 3.6 mg depot, followed in 28 days by one ZOLADEX 10.8 mg depot, should be administered.

2.2 Prostatic Carcinoma

For the management of advanced prostate cancer, ZOLADEX is intended for long-term administration unless clinically inappropriate.

2.3 Renal or Hepatic Impairment

No dosage adjustment is necessary for patients with renal or hepatic impairment.

2.4 Women

ZOLADEX 10.8 mg implant is not indicated in women as the data are insufficient to support reliable suppression of serum estradiol. For female patients requiring treatment with goserelin, refer to prescribing information for ZOLADEX 3.6 mg implant.

2.5 Administration Technique

The proper method of administration of ZOLADEX is described in the instructions that follow.

1. Put the patient in a comfortable position with the upper part of the body slightly raised. Prepare an area of the anterior abdominal wall below the navel line with an alcohol swab.
  NOTE: Caution should be taken while injecting ZOLADEX into the anterior abdominal wall due to the proximity of underlying inferior epigastric artery and its branches.
2. Examine the foil pouch and syringe for damage. Remove the syringe from the opened foil pouch and hold the syringe at a slight angle to the light. Check that at least part of the ZOLADEX implant is visible.
  NOTE: Do not remove the syringe by the plunger.
3. Grasp the blue plastic safety tab and pull away from the syringe, and discard. Remove needle cover. Unlike liquid injections, there is no need to remove air bubbles as attempts to do so may displace the ZOLADEX implant.
4. Holding the syringe around the protective sleeve, using an aseptic technique, pinch the skin of the patient's anterior abdominal wall below the navel line. With the bevel of the needle facing up, insert the needle at a 30 to 45 degree angle to the skin in one continuous deliberate motion until the protective sleeve touches the patient's skin.
  NOTE: The ZOLADEX syringe cannot be used for aspiration. If the hypodermic needle penetrates a large vessel, blood will be seen instantly in the syringe chamber. If a vessel is penetrated, withdraw the needle and inject with a new syringe elsewhere. Monitor patients for signs or symptoms of abdominal hemorrhage. Use extra care when administering ZOLADEX to patients with a low BMI and/or to patients receiving full dose anticoagulation [see Warnings and Precautions (5.7)].
5. Do not penetrate into muscle or peritoneum.
6. To administer the ZOLADEX implant and to activate the protective sleeve, grasp the barrel at the finger grip and depress the plunger until you cannot depress it any further. If the plunger is not depressed fully, the protective sleeve will NOT activate. When the protective sleeve ‘clicks’, the protective sleeve will automatically begin to slide to cover the needle.
  NOTE: The needle does not retract.
7. Withdraw the needle and allow protective sleeve to slide and cover needle. Dispose of the syringe in an approved sharps collector.
  NOTE: In the unlikely event of the need to surgically remove ZOLADEX, it may be localized by ultrasound.

3 DOSAGE FORMS AND STRENGTHS

ZOLADEX 10.8 mg implant is supplied as a sterile and totally biodegradable D,L-lactic and glycolic acids copolymer impregnated with 11.3 mg goserelin acetate equivalent to 10.8 mg of goserelin in a disposable syringe device fitted with a 14-gauge x 36 +/- 0.5 mm hypodermic siliconized needle with protective needle sleeve [SafeSystem® Syringe] (NDC 70720-951-30).

4 CONTRAINDICATIONS

4.1 Hypersensitivity

Anaphylactic reactions to ZOLADEX have been reported in the medical literature. ZOLADEX is contraindicated in those patients who have a known hypersensitivity to GnRH, GnRH agonist analogues or any of the components in ZOLADEX [see Warnings and Precautions (5.2)].

4.2 Pregnancy

Expected hormonal changes that occur with ZOLADEX treatment increase the risk for pregnancy loss. ZOLADEX may cause fetal harm when administered to a pregnant woman. If this drug is used during pregnancy, or if the patient becomes pregnant while taking this drug, the patient should be apprised of the potential hazard to the fetus [see Use in Specific Populations (8.1)].

5 WARNINGS AND PRECAUTIONS

5.1 Tumor Flare Phenomenon

Initially, ZOLADEX, like other GnRH agonists, causes transient increases in serum levels of testosterone. Transient worsening of symptoms, or the occurrence of additional signs and symptoms of prostatic cancer, may occasionally develop during the first few weeks of ZOLADEX treatment. A small number of patients may experience a temporary increase in bone pain, which can be managed symptomatically. As with other GnRH agonists, isolated cases of ureteral obstruction and spinal cord compression have been observed. If spinal cord compression or renal impairment secondary to ureteral obstruction develops, standard treatment of these complications should be instituted, and in extreme cases an immediate orchiectomy [see Adverse Reactions (6.1) and Patient Counseling Information (17.2)].

5.2 Hypersensitivity

Hypersensitivity, antibody formation and acute anaphylactic reactions have been reported with GnRH agonist analogues [see Contraindications (4.1)].

Of 115 women worldwide treated with ZOLADEX and tested for development of binding to goserelin following treatment with ZOLADEX, one patient showed low-titer binding to goserelin. On further testing of this patient's plasma obtained following treatment, her goserelin binding component was found not to be precipitated with rabbit antihuman immunoglobulin polyvalent sera. These findings suggest the possibility of antibody formation.

5.3 Hyperglycemia and Diabetes

Hyperglycemia and an increased risk of developing diabetes have been reported in men receiving GnRH agonists. Hyperglycemia may represent development of diabetes mellitus or worsening of glycemic control in patients with diabetes. Monitor blood glucose and/or glycosylated hemoglobin (HbA1c) periodically in patients receiving a GnRH agonist and manage with current practice for treatment of hyperglycemia or diabetes [see Patient Counseling Information (17.2)].

5.4 Cardiovascular Diseases

Increased risk of developing myocardial infarction, sudden cardiac death and stroke has been reported in association with use of GnRH agonists in men. The risk appears low based on the reported odds ratios, and should be evaluated carefully along with cardiovascular risk factors when determining a treatment for patients with prostate cancer. Patients receiving a GnRH agonist should be monitored for symptoms and signs suggestive of development of cardiovascular disease and be managed according to current clinical practice [see Patient Counseling Information (17.2)].

5.5 Severe Cutaneous Adverse Reactions

ZOLADEX can cause severe cutaneous adverse reactions (SCARs), including Stevens-Johnson syndrome/toxic epidermal necrolysis (SJS/TEN), drug reaction with eosinophilia and systemic symptoms (DRESS), and acute generalized exanthematous pustulosis (AGEP). SCARs, including SJS/TEN, DRESS, and AGEP, occurred in patients receiving ZOLADEX or other GnRH agonists; including cases with visceral involvement and/or requiring skin grafts [see Adverse Reactions (6.5) and Patient Counseling Information (17.1)].

Monitor patients for the development of SCARs. If a SCAR is suspected, interrupt ZOLADEX until the etiology of the reaction has been determined. Consultation with a dermatologist is recommended. If a SCAR is confirmed, or for other Grade 4 skin reactions, permanently discontinue ZOLADEX.

5.6 Effect on QT/QTc Interval

Androgen deprivation therapy may prolong the QT/QTc interval. Providers should consider whether the benefits of androgen deprivation therapy outweigh the potential risks in patients with congenital long QT syndrome, congestive heart failure, frequent electrolyte abnormalities, and in patients taking drugs known to prolong the QT interval. Electrolyte abnormalities should be corrected. Consider periodic monitoring of electrocardiograms and electrolytes.

5.7 Injection Site Injury

Injection site injury and vascular injury including pain, hematoma, hemorrhage and hemorrhagic shock, requiring blood transfusions and surgical intervention, have been reported with ZOLADEX. Extra care should be taken when administering ZOLADEX to patients with a low BMI and/or to patients receiving full anticoagulation [see Dosage and Administration (2.5) and Patient Counseling Information (17.2)].

6 ADVERSE REACTIONS

6.1 Clinical Trials

ZOLADEX has been found to be generally well tolerated in clinical trials. Adverse reactions reported in these trials were rarely severe enough to result in the patients' withdrawal from ZOLADEX treatment. As seen with other hormonal therapies, the most commonly observed adverse events during ZOLADEX therapy were due to the expected physiological effects from decreased testosterone levels. These included hot flashes, sexual dysfunction and decreased erections.

Tumor Flare Phenomenon: Initially, ZOLADEX, like other GnRH agonists, causes transient increases in serum levels of testosterone. A small percentage of patients experienced a temporary worsening of signs and symptoms, usually manifested by an increase in cancer-related pain which was managed symptomatically. Isolated cases of exacerbation of disease symptoms, either ureteral obstruction or spinal cord compression, occurred at similar rates in controlled clinical trials with both ZOLADEX and orchiectomy. The relationship of these events to therapy is uncertain [see Warnings and Precautions (5.1) and Patient Counseling Information (17.2)].

6.2 Stage B2-C Prostatic Carcinoma

Treatment with ZOLADEX and flutamide did not add substantially to the toxicity of radiation treatment alone. The following adverse experiences were reported during a multicenter clinical trial comparing ZOLADEX + flutamide + radiation versus radiation alone. The most frequently reported (greater than 5%) adverse experiences are listed below:

Table 1 ADVERSE EVENTS DURING ACUTE RADIATION THERAPY (within first 90 days of radiation therapy)
 | (n=231) flutamide + ZOLADEX + Radiation % All | (n=235) Radiation Only % All
Rectum/Large Bowel | 80 | 76
Bladder | 58 | 60
Skin | 37 | 37

Table 2 ADVERSE EVENTS DURING LATE RADIATION PHASE (after 90 days of radiation therapy)
 | (n=231) flutamide + ZOLADEX + Radiation % All | (n=235) Radiation Only % All
Diarrhea | 36 | 40
Cystitis | 16 | 16
Rectal Bleeding | 14 | 20
Proctitis | 8 | 8
Hematuria | 7 | 12

Additional adverse event data was collected for the combination therapy with radiation group over both the hormonal treatment and hormonal treatment plus radiation phases of the study. Adverse experiences occurring in more than 5% of patients in this group, over both parts of the study, were hot flashes (46%), diarrhea (40%), nausea (9%), and skin rash (8%).

6.3 Prostatic Carcinoma

Two controlled clinical trials using ZOLADEX 10.8 mg versus ZOLADEX 3.6 mg were conducted. During a comparative phase, patients were randomized to receive either a single 10.8 mg implant or three consecutive 3.6 mg implants every 4 weeks over weeks 0-12. During this phase, the only adverse event reported in greater than 5% of patients was hot flashes, with an incidence of 47% in the ZOLADEX 10.8 mg group and 48% in the ZOLADEX 3.6 mg group.

From weeks 12-48 all patients were treated with a 10.8 mg implant every 12 weeks. During this noncomparative phase, the following adverse events were reported in greater than 5% of patients:

Table 3 ADVERSE EVENTS WERE REPORTED IN GREATER THAN 5% OF PATIENTS
ADVERSE EVENTS | ZOLADEX 10.8 mg (n=157) %
Hot Flashes | 64
Pain (general) | 14
Gynecomastia | 8
Pelvic Pain | 6
Bone Pain | 6
Asthenia | 5

The following adverse events were reported in greater than 1%, but less than 5% of patients treated with ZOLADEX 10.8 mg implant every 12 weeks. Some of these are commonly reported in elderly patients.

WHOLE BODY – Abdominal pain, Back pain, Flu syndrome, Headache, Sepsis, Aggravation reaction

CARDIOVASCULAR – Angina pectoris, Cerebral ischemia, Cerebrovascular accident, Heart failure, Pulmonary embolus, Varicose veins

DIGESTIVE – Diarrhea, Hematemesis

ENDOCRINE – Diabetes mellitus

HEMATOLOGIC – Anemia

METABOLIC – Peripheral edema

NERVOUS SYSTEM – Dizziness, Paresthesia, Urinary retention

RESPIRATORY – Cough increased, Dyspnea, Pneumonia

SKIN – Herpes simplex, Pruritus

UROGENITAL – Bladder neoplasm, Breast pain, Hematuria, Impotence, Urinary frequency, Urinary incontinence, Urinary tract disorder, Urinary tract infection, Urination impaired

The following adverse events not already listed above were reported in patients receiving ZOLADEX 3.6 mg in other clinical trials. Inclusion does not necessarily represent a causal relationship to ZOLADEX 10.8 mg.

WHOLE BODY: Allergic reaction, Chills, Fever, Infection, Injection site reaction, Lethargy, Malaise

CARDIOVASCULAR: Arrhythmia, Chest pain, Hemorrhage, Hypertension, Migraine, Myocardial infarction, Palpitations, Peripheral vascular disorder, Tachycardia

DIGESTIVE: Anorexia, Constipation, Dry mouth, Dyspepsia, Flatulence, Increased appetite, Nausea, Ulcer, Vomiting

HEMATOLOGIC: Ecchymosis

METABOLIC: Edema, Gout, Hyperglycemia, Weight increase

MUSCULOSKELETAL: Arthralgia, Hypertonia, Joint disorder, Leg cramps, Myalgia, Osteoporosis

NERVOUS SYSTEM: Anxiety, Depression, Emotional lability, Headache, Insomnia, Nervousness, Somnolence, Thinking abnormal

RESPIRATORY: Bronchitis, Chronic obstructive pulmonary disease, Epistaxis, Rhinitis, Sinusitis, Upper respiratory infection, Voice alterations

SKIN: Acne, Alopecia, Dry skin, Hair disorders, Rash, Seborrhea, Skin discoloration, Sweating

SPECIAL SENSES: Amblyopia, Dry eyes

UROGENITAL: Breast tenderness, Decreased erections, Renal insufficiency, Sexual dysfunction, Urinary obstruction

6.4 Changes in Laboratory Values During Treatment

Plasma Enzymes: Elevation of liver enzymes (AST, ALT) have been reported in female patients exposed to ZOLADEX 3.6 mg (representing less than 1% of all patients). There was no other evidence of abnormal liver function. Causality between these changes and ZOLADEX have not been established.

Lipids: In a controlled trial in females, ZOLADEX 3.6 mg implant therapy resulted in a minor, but statistically significant effect on serum lipids (i.e., increases in LDL cholesterol of 21.3 mg/dL; increases in HDL cholesterol of 2.7 mg/dL; and triglycerides increased by 8.0 mg/dL).

6.5 Postmarketing Experience

The following adverse reactions have been identified during post-approval use of ZOLADEX. Because these reactions are reported voluntarily from a population of uncertain size, it is not always possible to reliably estimate their frequency or establish a causal relationship to drug exposure.

Hypercalcemia: In patients with bone metastases.

Bone Mineral Density: Osteoporosis, decreased bone mineral density and bone fracture in men [see Patient Counseling Information (17.2)].

Changes in Blood Pressure: Hypotension and hypertension have been reported. These changes are usually transient, resolving either during continued therapy or after cessation of therapy.

Pituitary Apoplexy and Tumors: Pituitary apoplexy (a clinical syndrome secondary to infarction of the pituitary gland) and pituitary adenoma have been diagnosed. Most of the pituitary apoplexy cases occurred within 2 weeks of the first dose, and some occurred within the first hour. In these cases, pituitary apoplexy has presented as sudden headache, vomiting, visual changes, ophthalmoplegia, altered mental status, and sometimes cardiovascular collapse. Immediate medical attention has been required. Pituitary tumors have been reported.

Acne: Usually within one month of starting treatment.

Skin reactions: SJS/TEN, DRESS, AGEP, dermatitis exfoliative, bullous dermatitis, and erythema multiforme.

Other Adverse Reactions: Psychotic disorders, convulsions and mood swings.

7 DRUG INTERACTIONS

No formal drug-drug interaction studies have been performed.

No drug interaction studies with other drugs have been conducted with ZOLADEX. No confirmed interactions have been reported between ZOLADEX and other drugs.

7.1 Drug/Laboratory Test Interactions

Administration of ZOLADEX in therapeutic doses results in suppression of the pituitary-gonadal system. Because of this suppression, diagnostic tests of pituitary-gonadotropic and gonadal functions conducted during treatment may show results which are misleading.

8 USE IN SPECIFIC POPULATIONS

8.1 Pregnancy

Based on mechanism of action in humans and findings of increased pregnancy loss in animal studies, ZOLADEX may cause fetal harm when administered to a pregnant woman. Expected hormone changes that occur with ZOLADEX treatment increase the risk for pregnancy loss. If this drug is used during pregnancy, or if the patient becomes pregnant while taking this drug, the patient should be apprised of the potential hazard to the fetus [see Contraindications (4.2)].

ZOLADEX crosses the placenta in rats and rabbits following subcutaneous administration. Administration of goserelin to pregnant rats and rabbits during organogenesis resulted in increased preimplantation loss and increased resorptions. When pregnant rats received goserelin throughout gestation and lactation, there was a dose-related increase in umbilical hernia in offspring. In additional reproduction studies in rats, goserelin decreased fetus and pup survival. Human dose/exposure multiples could not be calculated from available animal data.

Actual animal doses: rat (≥ 2 mcg/kg/day for pregnancy loss; ≥ 10 mcg/kg/day for umbilical hernia in offspring); rabbits (> 20 mcg/kg/day).

8.3 Nursing Mothers

It is not known if goserelin is excreted in human milk. Goserelin is excreted in the milk of lactating rats. Because many drugs are excreted in human milk, and because of the potential for serious adverse reactions in nursing infants from ZOLADEX, a decision should be made to either discontinue nursing or discontinue the drug, taking into account the importance of the drug to the mother.

8.4 Pediatric Use

Safety and effectiveness in pediatric patients have not been established.

8.5 Geriatric Use

There is no need for any dosage adjustment when administering ZOLADEX 10.8 mg to geriatric patients.

8.6 Renal Insufficiency

In clinical trials with the solution formulation of goserelin, subjects with impaired renal function (creatinine clearance < 20 mL/min) had a serum elimination half-life of 12.1 hours compared to 4.2 hours for subjects with normal renal function (creatinine clearance > 70 mL/min). However, there was no evidence for any accumulation of goserelin on multiple dosing of the ZOLADEX 10.8 mg depot to subjects with impaired renal function. There was no evidence for any increase in incidence of adverse events in renally impaired patients administered the 10.8 mg depot. These data indicate that there is no need for any dosage adjustment when administering ZOLADEX 10.8 mg to subjects with impaired renal function.

8.7 Hepatic Insufficiency

The total body clearances and serum elimination half-lives were similar between normal subjects and patients with moderate hepatic impairment (alanine transaminase < 3xULN and asparate aminotransferase < 3xULN) when treated with a 250 mcg subcutaneous formulation of goserelin. This pharmacokinetic study indicates that no dose adjustment is needed in patients with moderately impaired liver function. There is no pharmacokinetic data with goserelin in patients with severe hepatic insufficiency.

8.8 Body Weight

A decline of approximately 1 to 2.5% in the AUC after administration of a 10.8 mg depot was observed with a kilogram increase in body weight. In obese patients who have not responded clinically, testosterone levels should be monitored closely.

10 OVERDOSAGE

The pharmacologic properties of ZOLADEX and its mode of administration make accidental or intentional overdosage unlikely. There is no experience of overdosage from clinical trials. Animal studies indicate that no increased pharmacologic effect occurred at higher doses or more frequent administration. Subcutaneous doses of the drug as high as 1 mg/kg/day in rats and dogs did not produce any nonendocrine related sequelae; this dose is up to 250 times the estimated human daily dose based on the body surface area. If overdosage occurs, it should be managed symptomatically.

11 DESCRIPTION

ZOLADEX (goserelin implant) is a GnRH agonist. Goserelin acetate is chemically described as an acetate salt of [D-Ser(But)^6,Azgly^10]. Its chemical structure is pyro-Glu-His-Trp-Ser-Tyr-D-Ser(But)-Leu-Arg-Pro-Azgly-NH2 acetate [C59H84N18O14·(C2H4O2)x where x = 1 to 2.4].

Goserelin acetate is an off-white powder with a molecular weight of 1269 Daltons (free base). It is freely soluble in glacial acetic acid. It is soluble in water, 0.1M hydrochloric acid, 0.1M sodium hydroxide, dimethylformamide and dimethyl sulfoxide. Goserelin acetate is practically insoluble in acetone, chloroform and ether.

ZOLADEX 10.8 mg implant is supplied as a sterile, biodegradable product containing 11.3 mg goserelin acetate equivalent to 10.8 mg of goserelin. ZOLADEX is designed for subcutaneous implantation with continuous release over a 12-week period. Goserelin acetate, containing up to 10% goserelin-related substances, is dispersed in a matrix of D,L-lactic and glycolic acids copolymer (to a total implant weight of 36.0 mg, containing less than 2% total acetic acid) and presented as a sterile, white to cream colored 1.5 mm diameter cylinder, preloaded in a special single-use syringe with a 14-gauge x 36 +/- 0.5 mm siliconized needle with protective needle sleeve (SafeSystem® Syringe) in a sealed, light- and moisture-proof, aluminum foil laminate pouch containing a desiccant capsule.

Studies of the D,L-lactic and glycolic acids copolymer have indicated that it is completely biodegradable and has no demonstrable antigenic potential.

ZOLADEX is also supplied as a sterile, biodegradable product containing goserelin acetate equivalent to 3.6 mg of goserelin designed for administration every 28 days.

12 CLINICAL PHARMACOLOGY

12.1 Mechanism of Action

ZOLADEX is a synthetic decapeptide analogue of GnRH. ZOLADEX acts as an inhibitor of pituitary gonadotropin secretion when administered in the biodegradable formulation.

In animal and in vitro studies, administration of goserelin resulted in the regression or inhibition of growth of the hormonally sensitive dimethylbenzanthracene (DMBA)-induced rat mammary tumor and Dunning R3327 prostate tumor.

12.2 Pharmacodynamics

Following initial administration, ZOLADEX causes an initial increase in serum luteinizing hormone (LH) and follicle stimulating hormone (FSH) levels with subsequent increases in serum levels of testosterone. Chronic administration of ZOLADEX leads to sustained suppression of pituitary gonadotropins, and serum levels of testosterone consequently fall into the range normally seen in surgically castrated men approximately 21 days after initiation of therapy. This leads to accessory sex organ regression.

In clinical trials using ZOLADEX 3.6 mg with follow-up of more than 2 years, suppression of serum testosterone to castrate levels has been maintained for the duration of therapy.

12.3 Pharmacokinetics

Absorption

The pharmacokinetics of ZOLADEX have been determined in healthy male volunteers and patients. In healthy males, radiolabeled goserelin was administered as a single 250 mcg (aqueous solution) dose by the subcutaneous route. The absorption of radiolabeled drug was rapid, and the peak blood radioactivity levels occurred between 0.5 and 1.0 hour after dosing.

The overall pharmacokinetic profile of goserelin following administration of a ZOLADEX 10.8 mg depot to patients with prostate cancer was determined. The initial release of goserelin from the depot was relatively rapid resulting in a peak concentration at 2 hours after dosing. From Day 4 until the end of the 12-week dosing interval, the sustained release of goserelin from the depot produced reasonably stable systemic exposure. Mean (Standard Deviation) pharmacokinetic data are presented in Table 4. There is no clinically significant accumulation of goserelin following administration of four depots administered at 12-week intervals.

Table 4 GOSERELIN PHARMACOKINETIC PARAMETERS FOR THE 10.8 MG DEPOT
Parameter | N | Mean | (SD)
Systemic clearance (mL/min) | 41 | 121 | (42.4)
Cmax (ng/mL) | 41 | 8.85 | (2.83)
Tmax (h) | 41 | 1.80 | (0.34)
Cmin (ng/mL) | 44 | 0.37 | (0.21)
SD = standard deviation

Serum goserelin concentrations in prostate cancer patients administered three 3.6 mg depots followed by one 10.8 mg depot are displayed in Figure 1. The profiles for both formulations are primarily dependent upon the rate of drug release from the depots. For the 3.6 mg depot, mean concentrations gradually rise to reach a peak of about 3 ng/mL at around 15 days after administration and then decline to approximately 0.5 ng/mL by the end of the treatment period. For the 10.8 mg depot, mean concentrations increase to reach a peak of about 8 ng/mL within the first 24 hours and then decline rapidly up to Day 4. Thereafter, mean concentrations remain relatively stable in the range of about 0.3 to 1 ng/mL up to the end of the treatment period.

Administration of four ZOLADEX 10.8 mg depots to patients with prostate cancer resulted in testosterone levels that were suppressed to and maintained within the range normally observed in surgically castrated men (0 – 1.73 nmol/L or 0-50 ng/dL), over the dosing interval in approximately 91% (145/160) of patients studied. In 6 of 15 patients that escaped from castrate range, serum testosterone levels were maintained below 2.0 nmol/L (58 ng/dL) and in only one of the 15 patients did the depot completely fail to maintain serum testosterone levels to within the castrate range over a 336-day period (4 depot injections). In the 8 additional patients, a transient escape was followed 14 days later by a level within the castrate range.

Distribution

The apparent volume of distribution determined after subcutaneous administration of 250 mcg aqueous solution of goserelin was 44.1 ± 13.6 liters for healthy males. The plasma protein binding of goserelin was found to be 27%.

Metabolism

Metabolism of goserelin, by hydrolysis of the C-terminal amino acids, is the major clearance mechanism. The major circulating component in serum appeared to be 1–7 fragment, and the major component present in urine of one healthy male volunteer was 5-10 fragment. The metabolism of goserelin in humans yields a similar but narrow profile of metabolites to that found in other species. All metabolites found in humans have also been found in toxicology species.

Excretion

Clearance of goserelin following subcutaneous administration of a radiolabeled solution of goserelin was very rapid and occurred via a combination of hepatic and urinary excretion. More than 90% of a subcutaneous radiolabeled solution formulation dose of goserelin was excreted in urine. Approximately 20% of the dose recovered in urine was accounted for by unchanged goserelin.

13 NONCLINICAL TOXICOLOGY

13.1 Carcinogenesis, Mutagenesis, Impairment of Fertility

Subcutaneous implantation of goserelin in male and female rats once every 4 weeks for 1 year and recovery for 23 weeks at doses of about 80 and 150 mcg/kg (males) and 50 and 100 mcg/kg (females) daily resulted in an increased incidence of pituitary adenomas. An increased incidence of pituitary adenomas was also observed following subcutaneous implant of goserelin in rats at similar dose levels for a period of 72 weeks in males and 101 weeks in females. The relevance of the rat pituitary adenomas to humans has not been established. Subcutaneous implants of goserelin every 3 weeks for 2 years delivered to mice at doses of up to 2400 mcg/kg/day resulted in an increased incidence of histiocytic sarcoma of the vertebral column and femur. Human dose/exposure multiples could not be calculated from available animal data.

Mutagenicity tests using bacterial and mammalian systems for point mutations and cytogenetic effects have provided no evidence for mutagenic potential.

Administration of goserelin led to changes that were consistent with gonadal suppression in both male and female rats as a result of its endocrine action. In male rats administered 500-1000 mcg/kg/day, a decrease in weight and atrophic histological changes were observed in the testes, epididymis, seminal vesicle and prostate gland with complete suppression of spermatogenesis. In female rats administered 50-1000 mcg/kg/day, suppression of ovarian function led to decreased size and weight of ovaries and secondary sex organs; follicular development was arrested at the antral stage and the corpora lutea were reduced in size and number. Except for the testes, almost complete histologic reversal of these effects in males and females was observed several weeks after dosing was stopped; however, fertility and general reproductive performance were reduced in those that became pregnant after goserelin was discontinued. Fertile matings occurred within 2 weeks after cessation of dosing, even though total recovery of reproductive function may not have occurred before mating took place; and, the ovulation rate, the corresponding implantation rate, and number of live fetuses were reduced.

Based on histological examination, drug effects on reproductive organs were reversible in male and female dogs administered 107-214 mcg/kg/day goserelin when drug treatment was stopped after continuous administration for 1 year. Human dose/exposure multiples could not be calculated from available animal data.

14 CLINICAL STUDIES

14.1 Stage B2-C Prostatic Carcinoma

The effects of hormonal treatment combined with radiation were studied in 466 patients (231 ZOLADEX + flutamide + radiation, 235 radiation alone) with bulky primary tumors confined to the prostate (stage B2) or extending beyond the capsule (stage C), with or without pelvic node involvement.

In this multicentered, controlled trial, administration of ZOLADEX (3.6 mg depot) and flutamide capsules (250 mg t.i.d.) prior to and during radiation was associated with a significantly lower rate of local failure compared to radiation alone (16% vs 33% at 4 years, P<0.001). The combination therapy also resulted in a trend toward reduction in the incidence of distant metastases (27% vs 36% at 4 years, P=0.058). Median disease-free survival was significantly increased in patients who received complete hormonal therapy combined with radiation as compared to those patients who received radiation alone (4.4 vs 2.6 years, P<0.001). Inclusion of normal PSA level as a criterion for disease-free survival also resulted in significantly increased median disease-free survival in patients receiving the combination therapy (2.7 vs 1.5 years, P<0.001).

14.2 Prostatic Carcinoma

In two controlled clinical trials, 160 patients with advanced prostate cancer were randomized to receive either one 3.6 mg ZOLADEX implant every four weeks or a single 10.8 mg ZOLADEX implant every 12 weeks. Mean serum testosterone suppression was similar between the two arms. PSA falls at three months were 94% in patients who received the 10.8 mg implant and 92.5% in patients that received three 3.6 mg implants.

Periodic monitoring of serum testosterone levels should be considered if the anticipated clinical or biochemical response to treatment has not been achieved. A clinical outcome similar to that produced with the use of the 3.6 mg implant administered every 28 days is predicted with ZOLADEX 10.8 mg implant administered every 12 weeks (84 days). Total testosterone was measured by the DPC Coat-A-Count radioimmunoassay method which, as defined by the manufacturers, is highly specific and accurate. Acceptable variability of approximately 20% at low testosterone levels has been demonstrated in the clinical studies performed with the ZOLADEX 10.8 mg depot.

16 HOW SUPPLIED/STORAGE AND HANDLING

ZOLADEX 10.8 mg implant is supplied as a sterile and totally biodegradable D,L-lactic and glycolic acids copolymer impregnated with 11.3 mg goserelin acetate equivalent to 10.8 mg of goserelin in a disposable syringe device fitted with a 14-gauge x 36 +/- 0.5 mm siliconized hypodermic needle with protective sleeve [SafeSystem® Syringe] (NDC 70720-951-30). The unit is sterile and comes in a sealed, light- and moisture-proof, aluminum foil laminate pouch containing a desiccant capsule. Store at room temperature (do not exceed 25°C [77°F]).

17 PATIENT COUNSELING INFORMATION

17.1 Severe Cutaneous Adverse Reactions

Inform patients that severe cutaneous adverse reactions (SCARs), including Stevens-Johnson syndrome (SJS), toxic epidermal necrolysis (TEN), drug reaction with eosinophilia and systemic symptoms (DRESS), and acute generalized exanthematous pustulosis (AGEP), which may be life threatening or fatal, may occur during treatment with ZOLADEX. Advise patients to contact their healthcare provider or seek medical attention right away if they experience signs or symptoms of SCARs, e.g., a prodrome of fever, flu-like symptoms, mucosal lesions, progressive skin rash, or lymphadenopathy [see Warnings and Precautions (5.5) and Adverse Reactions (6.5)].

17.2 Males

The use of ZOLADEX in patients at particular risk of developing ureteral obstruction or spinal cord compression should be considered carefully and the patients monitored closely during the first month of therapy. Patients with ureteral obstruction or spinal cord compression should have appropriate treatment prior to initiation of ZOLADEX therapy [see Warnings and Precautions (5.1) and Adverse Reactions (6.1)].

The use of GnRH agonists may cause a reduction in bone mineral density. In men, data suggest the use of a bisphosphonate in combination with a GnRH agonist may reduce bone mineral loss [see Adverse Reactions (6.5)].

Patients should be informed that diabetes, or loss of glycemic control in patients with pre-existing diabetes, has been reported during treatment with GnRH agonists, including ZOLADEX. Therefore, consideration should be given to monitoring blood glucose and/or glycosylated hemoglobin (HbA1c) periodically in patients receiving ZOLADEX [see Warnings and Precautions (5.3)].

A small increased risk of developing myocardial infarction, sudden cardiac death and stroke has been reported in association with use of GnRH agonists in men. Patients receiving a GnRH agonist should be monitored for symptoms and signs suggestive of development of cardiovascular disease and be managed according to current clinical practice [see Warnings and Precautions (5.4)].

Injection site injury has been reported following injection of ZOLADEX. Inform patients to contact their doctor immediately if they experience any of the following symptoms: abdominal pain, abdominal distension, dyspnea, dizziness, hypotension and/or any altered levels of consciousness [see Warnings and Precautions (5.7)].

ZOLADEX® and SAFESYSTEM® are registered trademarks of AstraZeneca or its affiliates and are used herein under license.

©2025 TerSera Therapeutics LLC

Distributed by: TerSera Therapeutics LLC, Deerfield, IL 60015

TerSera®
therapeutics

Principal Display Panel - Zoladex Carton Label

NDC 70720-951-30

Zoladex®10.8mg
goserelin implant

10.8 mg goserelin
Equivalent to 11.3 mg goserelin acetate

One Single-Use Syringe
For Subcutaneous Injection

For use in men with prostate cancer only